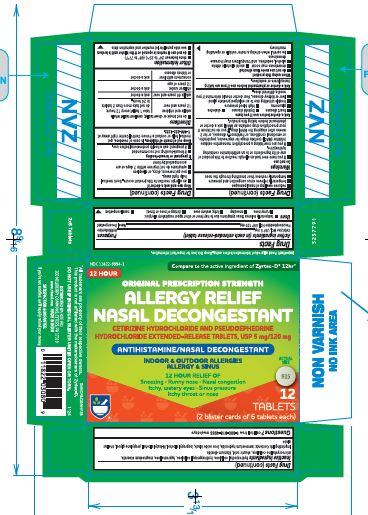 DRUG LABEL: Allergy relief-D
NDC: 11822-9994 | Form: TABLET, FILM COATED, EXTENDED RELEASE
Manufacturer: RITE AID
Category: otc | Type: HUMAN OTC DRUG LABEL
Date: 20250102

ACTIVE INGREDIENTS: CETIRIZINE HYDROCHLORIDE 5 mg/1 1; PSEUDOEPHEDRINE HYDROCHLORIDE 120 mg/1 1
INACTIVE INGREDIENTS: HYDROXYPROPYL CELLULOSE (1600000 WAMW); HYPROMELLOSE, UNSPECIFIED; MAGNESIUM STEARATE; MICROCRYSTALLINE CELLULOSE; STEARIC ACID; TITANIUM DIOXIDE; AMMONIA; FERROSOFERRIC OXIDE; ISOPROPYL ALCOHOL; BUTYL ALCOHOL; PROPYLENE GLYCOL; SHELLAC; HYDROXYETHYL CELLULOSE (4000 MPA.S AT 1%)

Allergy relief-D

Important: Read all product information before using. Keep this box for important information.

Drug Facts

ACTIVE INGREDIENT

PURPOSE

Active ingredients (in each extended-release tablet) | Purposes
Cetirizine HCl, USP 5 mg | Antihistamine
Pseudoephedrine HCl, USP 120 mg | Nasal Decongestant

Uses

- temporarily relieves these symptoms due to hay fever or other upper respiratory allergies:
  - runny nose
  - sneezing
  - itchy, watery eyes
  - itching of nose or throat
  - nasal congestion
- reduces swelling of nasal passages
- temporarily relieves sinus congestion and pressure
- temporarily restores freer breathing through the nose

Warnings

Do not use

- if you have ever had an allergic reaction to this product or any of its ingredients or to an antihistamine containing hydroxyzine.
- if you are now taking a prescription monoamine oxidase inhibitor (MAOI) (certain drugs for depression, psychiatric, or emotional conditions, or Parkinson's disease), or for 2 weeks after stopping the MAOI drug. If you do not know if your prescription drug contains an MAOI, ask a doctor or pharmacist before taking this product.

Ask a doctor before use if you have

- heart disease
- thyroid disease
- diabetes
- glaucoma
- high blood pressure
- trouble urinating due to an enlarged prostate gland
- liver or kidney disease. Your doctor should determine if you need a different dose.

Ask a doctor or pharmacist before use if you aretaking tranquilizers or sedatives.

When using this product

- do not use more than directed
- drowsiness may occur
- avoid alcoholic drinks
- alcohol, sedatives, and tranquilizers may increase drowsiness
- be careful when driving a motor vehicle or operating machinery

Stop use and ask a doctor if

- an allergic reaction to this product occurs. Seek medical help right away.
- you get nervous, dizzy, or sleepless
- symptoms do not improve within 7 days or are accompanied by fever

If pregnant or breast-feeding

- if breast-feeding: not recommended
- if pregnant: ask a health professional before use.

Keep out of reach of children.In case of overdose, get medical help or contact a Poison Control Center right away at 1-800-222-1222.

Directions

- do not break or chew tablet; swallow tablet whole

adults and children 12 years and over | take 1 tablet every 12 hours; do not take more than 2 tablets in 24 hours.
adults 65 years and over | ask a doctor
children under 12 years of age | ask a doctor
consumers with liver or kidney disease | ask a doctor

Other information

- store between 20° to 25°C (68° to 77°F)
- do not use if carton is opened or if the blister unit is broken
- see side panel for lot number and expiration date

Inactive ingredients

hydroxyethyl cellulose, hydroxypropyl cellulose, hypromellose, magnesium stearate, microcrystalline cellulose, stearic acid, titanium dioxide

Imprinting Ink Contents: ammonium hydroxide, iron oxide black, isopropyl alcohol, N-butyl alcohol, propylene glycol, shellac glaze

Questions?

call toll free 1-800-818-4555weekdays

DISTRIBUTED BY: RITE AID,
200 NEWBERRY COMMONS, ETTERS, PA 17319

PRINCIPAL DISPLAY PANEL - 12 Tablet Blister Card Carton

NDC 11822-9994-1
12 HOUR

Compare to the active ingredient of Zyrtec-D®12hr*

ORIGINAL PRESCRIPTION STRENGTH

ALLERGY RELIEF
NASAL DECONGESTANT

CETIRIZINE HYDROCHLORIDE AND PSEUDOEPHEDRINE
HYDROCHLORIDE EXTENDED-RELEASE TABLETS, USP 5 mg/120 mg

ANTIHISTAMINE/NASAL DECONGESTANT

INDOOR & OUTDOOR ALLERGIES
ALLERGY & SINUS

12 HOUR RELIEF OF
Sneezing • Runny nose • Nasal congestion
Itchy, watery eyes • Sinus pressure
Itchy throat or nose

ACTUAL
SIZE

12
TABLETS
(2 blister cards of 6 tablets each)